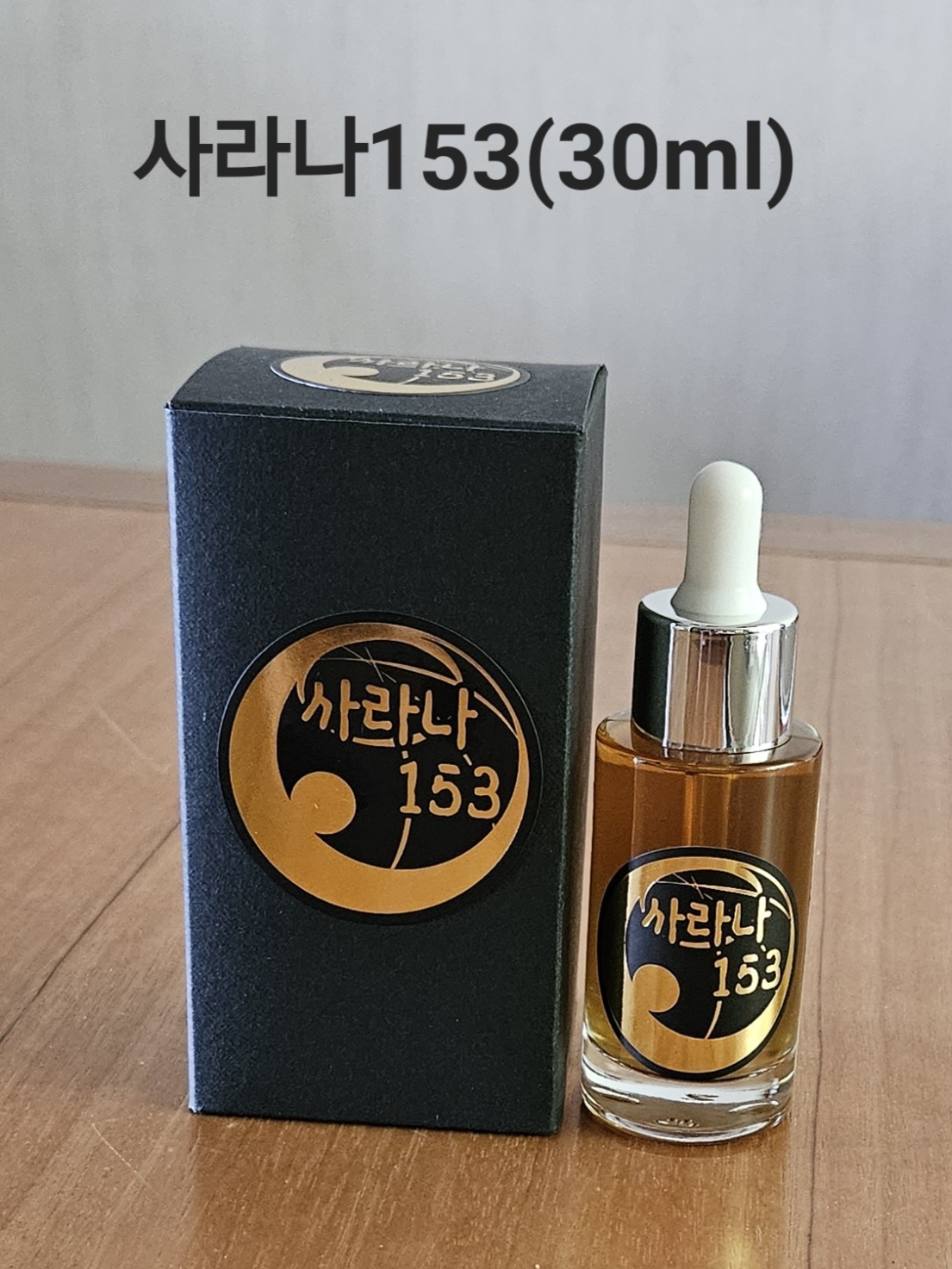 DRUG LABEL: SALANA 153 (Blood circulation, Cytothesis, Thrombolysis, Immunity boost, An antitumor, Antiinflammatory, Regulatory action, Inhibitory action, Exocytosis)
NDC: 77008-1536 | Form: LIQUID
Manufacturer: BIOHERB Co., Ltd.
Category: otc | Type: HUMAN OTC DRUG LABEL
Date: 20250528

ACTIVE INGREDIENTS: SHIITAKE MUSHROOM 15 g/100 g
INACTIVE INGREDIENTS: PINE NEEDLE OIL (PINUS MUGO) 7 g/100 g

SALANA 153 (Blood circulation, Cytothesis, Thrombolysis, Immunity boost, An antitumor, Antiinflammatory, Regulatory action, Inhibitory action, Exocytosis)

INDICATIONS AND USAGE

Blood circulation improvement. Thrombolysis

Promote cell restoration

Immunity boost

An anti tumor

Antiinflammatory

KEEP OUT OF THE REACH OF CHILDREN.

DOSAGE AND ADMINISTRATION

Norugun dew mushroom

WARNINGS

Keep out of children

PURPOSE

Norugung dew mushroom

Inactive ingredients:

Norugung dew mushroom

Active Ingredients

SHIITAKE MUSHROOM

RECENT MAJOR CHANGES

Newly added product